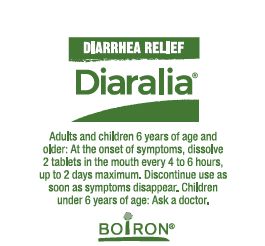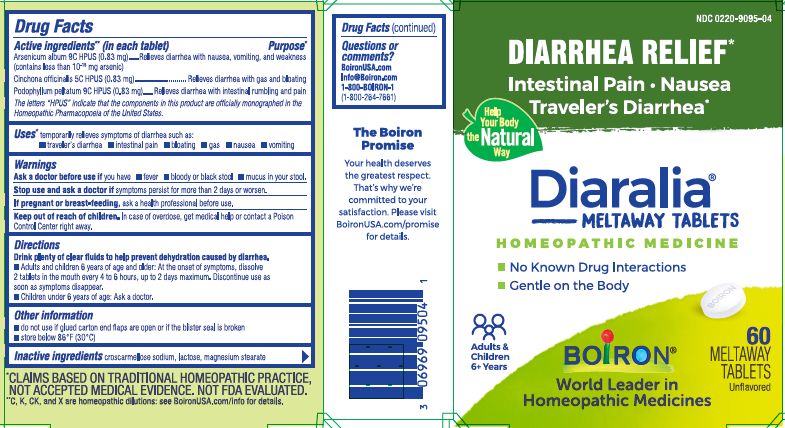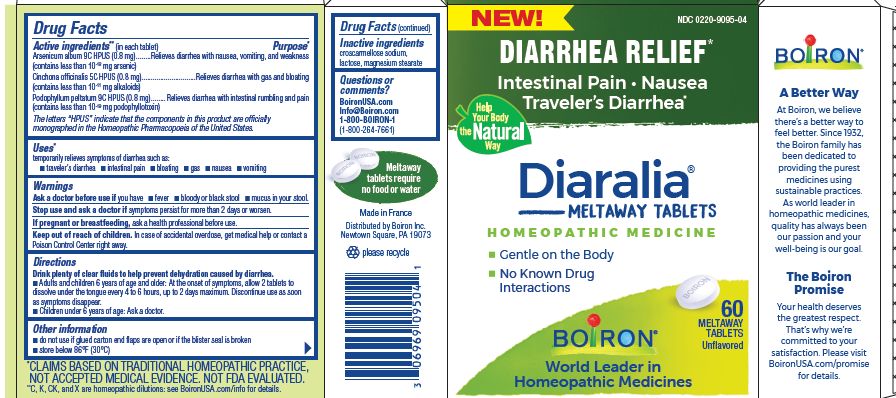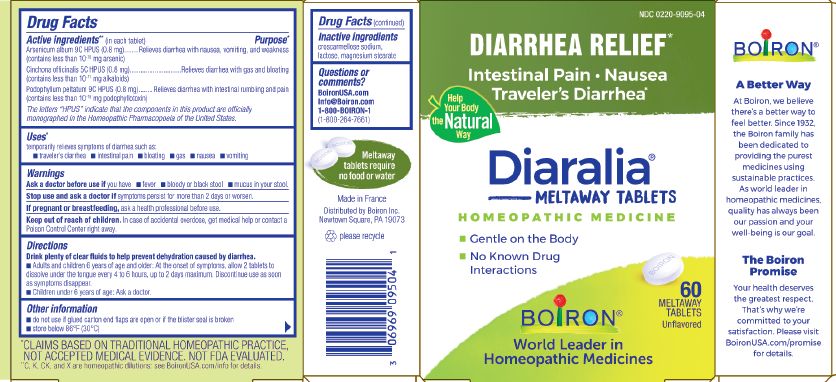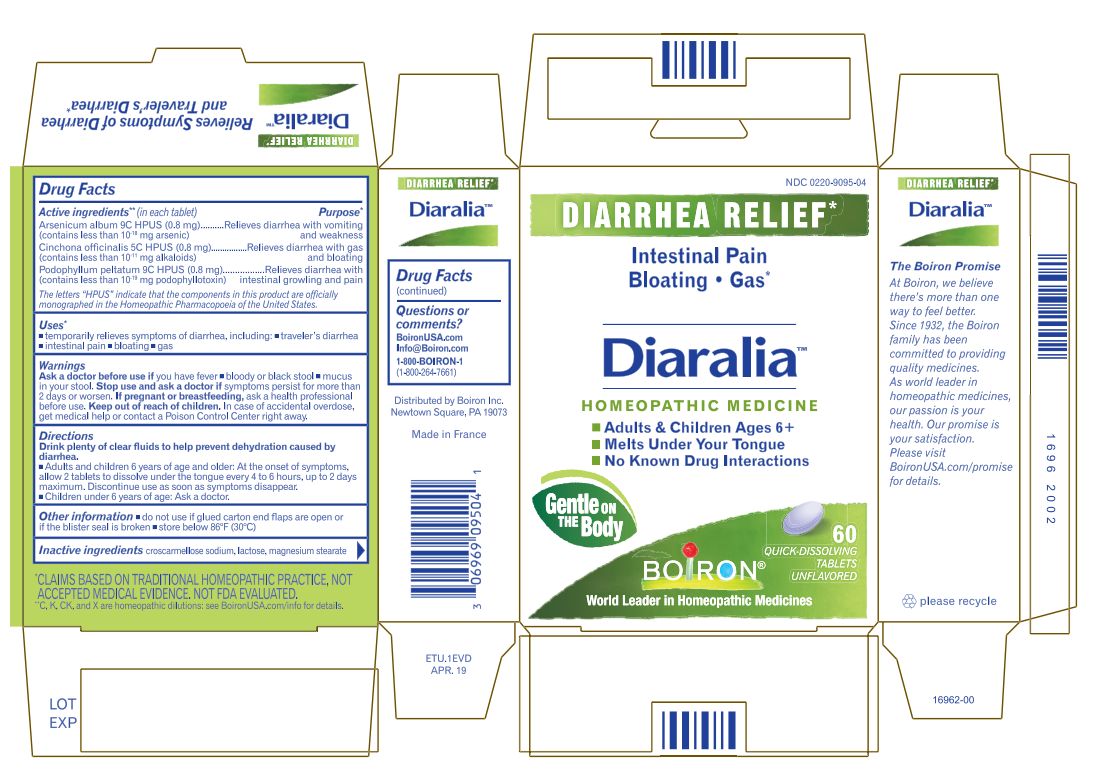 DRUG LABEL: DIARALIA
NDC: 0220-9095 | Form: TABLET
Manufacturer: BOIRON
Category: homeopathic | Type: HUMAN OTC DRUG LABEL
Date: 20230510

ACTIVE INGREDIENTS: PODOPHYLLUM 9 [hp_C]/1 1; CINCHONA OFFICINALIS BARK 5 [hp_C]/1 1; ARSENIC TRIOXIDE 9 [hp_C]/1 1
INACTIVE INGREDIENTS: CROSCARMELLOSE SODIUM; MAGNESIUM STEARATE; LACTOSE, UNSPECIFIED FORM

DIARALIA

Active ingredients** (in each tablet)

Arsenicum album 9C HPUS (0.83 mg)

Cinchona officinalis 5C HPUS (0.83 mg)

Podophyllum peltatum 9C HPUS (0.83 mg)

The letters "HPUS" indicate that the components in this product are officially monographed in the Homeopathic Pharmacopoeia of the United States.

Uses*

temporarily relieves symptoms of diarrhea such as:

- traveler's diarrhea
- intestinal pain
- bloating
- gas
- nausea
- vomiting

Purpose*

Arsenicum album 9C HPUS (0.83 mg) ... Relieves diarrhea with nausea, vomiting, and weakness. (contains less that 10^-18 mg arsenic)

Cinchona officinalis 5C HPUS (0.83 mg) ... Relieves diarrhea with gas and bloating

Podophyllum peltatum 9C HPUS (0.83 mg) ... Relieves diarrhea with intestinal rumbling and pain

Ask a doctor before use if you have

fever

bloody or black stool

mucus in your stool.

Stop use and ask a doctor if symptoms persist for more than 2 days or worsen.

PREGNANCY OR BREAST FEEDING

If pregnant or breast-feeding, ask a health professional before use.

Keep out of reach of children. In case of overdose, get medical help or contact a Poison Control Center right away.

DOSAGE AND ADMINISTRATION

Drink plenty of clear fluids to help prevent dehydration caused by diarrhea.

- Adults and children 6 years of age and older: At the onset of symptoms, dissolve 2 tablets in the mouth every 4 to 6 hours, up to 2 days maximum. Discontinue use as soon as symptoms disappear.
- Children under 6 years of age: Ask a doctor.

do not use if glued carton end flaps are open or if the blister seal is broken.

store below 86° F (30° C)

60 Meltaway Tablets

No Known Drug Interactions

Diarrhea Relief*

Intestinal Pain Nausea Traveler's Diarrhea*

*CLAIMS BASED ON TRADITIONAL HOMEOPATHIC PRACTICE NOT ACCEPTED MEDICAL EVIDENCE. NOT FDA EVALUATED.
*C,K,CK, and X are homeopathic dilutions: see BoironUSA.com/info for details.

INACTIVE INGREDIENT

lactose, croscarmellose sodium, magnesium stearate

QUESTIONS

1-800-BOIRON-1 (1-800-264-7661),
BoironUSA.com Info@boiron.com
Distributed by Boiron, Inc. Newtown Square, PA 19073